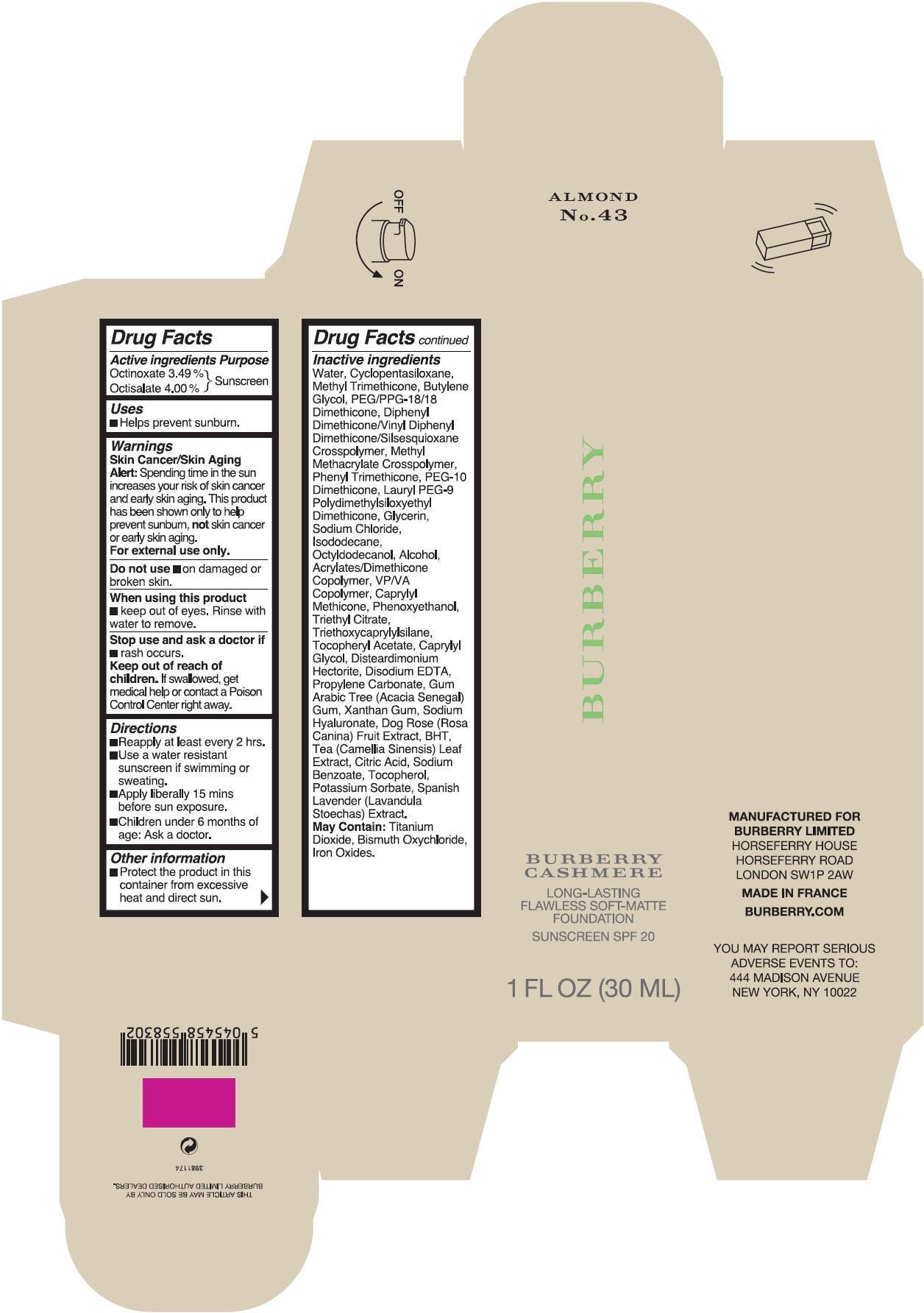 DRUG LABEL: Burberry Cashmere Long-Lasting Flawless Soft-Matte Foundation Sunscreen SPF20 Almond
NDC: 69038-036 | Form: CREAM
Manufacturer: Burberry Limited
Category: otc | Type: HUMAN OTC DRUG LABEL
Date: 20171225

ACTIVE INGREDIENTS: OCTINOXATE 34.9 mg/1 mL; OCTISALATE 40 mg/1 mL
INACTIVE INGREDIENTS: COPOVIDONE K25-31; WATER; CYCLOMETHICONE 5; METHYL TRIMETHICONE; BUTYLENE GLYCOL; PEG/PPG-18/18 DIMETHICONE; PHENYL TRIMETHICONE; LAURYL PEG-9 POLYDIMETHYLSILOXYETHYL DIMETHICONE; GLYCERIN; SODIUM CHLORIDE; ISODODECANE; OCTYLDODECANOL; ALCOHOL; CAPRYLYL TRISILOXANE; PHENOXYETHANOL; TRIETHYL CITRATE; TRIETHOXYCAPRYLYLSILANE; .ALPHA.-TOCOPHEROL ACETATE; CAPRYLYL GLYCOL; DISTEARDIMONIUM HECTORITE; EDETATE DISODIUM ANHYDROUS; PROPYLENE CARBONATE; XANTHAN GUM; HYALURONATE SODIUM; BUTYLATED HYDROXYTOLUENE; TEA LEAF; CITRIC ACID MONOHYDRATE; SODIUM BENZOATE; TOCOPHEROL; POTASSIUM SORBATE; FERRIC OXIDE RED

Burberry Cashmere Long-Lasting Flawless Soft-Matte Foundation Sunscreen SPF20 Almond No. 43

Active ingredients

Octinoxate 3.49%

Octisalate 4.00%

Purpose

Sunscreen

Uses

- Helps Prevent Sunburn.

Warnings

Skin Cancer/Skin Aging Alert: Spending time in the sun increases your risk of skin cancer and early skin aging. This product has been shown only to help prevent sunburn, not skin cancer or early skin aging.

For external use only.

Do not use

- on damaged or broken skin.

When using this product

- keep out of eyes. Rinse with water to remove.

Stop use and ask a doctor if

- rash occurs.

Keep out of reach of children.

If swallowed, get medical help or contact a Poison Control Center right away.

Directions

- Reapp ly at least every 2 hrs.
- Use a water resistant sunscreen if swimming or sweating.
- Apply liberal ly 15 mins before sun exposure.
- Children under 6 months of age: Ask a doctor.

Other information

- Protect the product in this container from excessive heat and direct sun.

Inactive ingredients

Water, Cyclopentasiloxane, Methyl Trimethicone, Butylene Glycol, PEG/PPG-18/18 Dimethicone, Diphenyl Dimethicone/Vinyl Diphenyl Dimethicone/Silsesquioxane Crosspolymer, Methyl Methacrylate Crosspolymer, Phenyl Trimethicone, PEG-10 Dimethicone, Lauryl PEG-9 Polydimethylsiloxyethyl Dimethicone, Glycerin, Sodium Chloride, Isododecane, Octyldodecanol, Alcohol, Acrylates/Dimethicone Copolymer, VP/VA Copolymer, Caprylyl Methicone, Phenoxyethanol, Triethyl Citrate, Triethoxycaprylylsilane, Tocopheryl Acetate, Caprylyl Glycol,
Disteardimonium Hectorite, Disodium EDTA, Propylene Carbonate, Gum Arabic Tree (Acacia Senegal) Gum, Xanthan Gum, Sodium Hyaluronate, Dog Rose (Rosa Canina) Fruit Extract, BHT, Tea (Camellia Sinensis) Leaf Extract, Citric Acid, Sodium Benzoate, Tocopherol, Potassium Sorbate, Spanish Lavender (Lavandula Stoechas) Extract. May Contain: Titanium Dioxide, Bismuth Oxychloride, Iron Oxides.